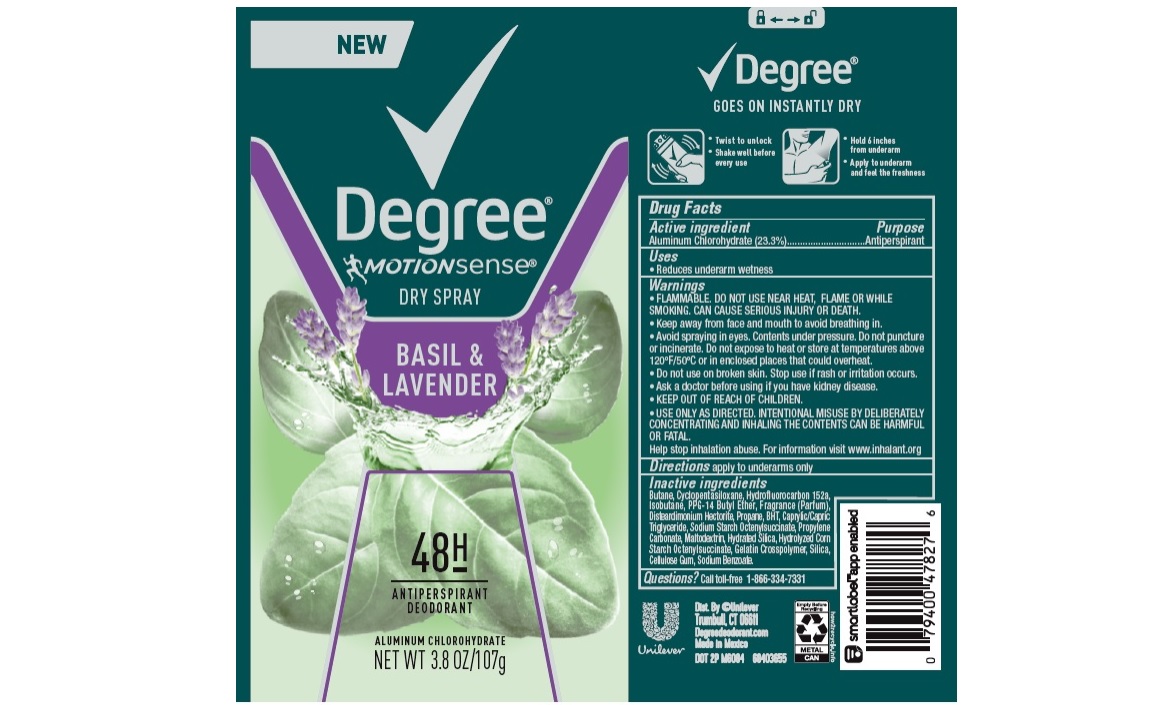 DRUG LABEL: Degree
NDC: 64942-1769 | Form: AEROSOL, SPRAY
Manufacturer: Conopco, Inc. d/b/a Unilever
Category: otc | Type: HUMAN OTC DRUG LABEL
Date: 20241110

ACTIVE INGREDIENTS: ALUMINUM CHLOROHYDRATE 23.3 g/100 g
INACTIVE INGREDIENTS: PPG-14 BUTYL ETHER; BUTANE; 1,1-DIFLUOROETHANE; CYCLOMETHICONE 5; ISOBUTANE; DISTEARDIMONIUM HECTORITE; MEDIUM-CHAIN TRIGLYCERIDES; PROPANE; BUTYLATED HYDROXYTOLUENE; CARBOXYMETHYLCELLULOSE SODIUM; PROPYLENE CARBONATE; HYDRATED SILICA; MALTODEXTRIN; SILICON DIOXIDE; SODIUM BENZOATE

Degree Motionsense Dry Spray Basil & Lavender 48H Antiperspirant Deodorant

DEGREE MOTIONSENSE DRY SPRAY BASIL & LAVENDER 48H ANTIPERSPIRANT DEODORANT - aluminum chlorohydrate aerosol, spray

Degree Motionsense Dry Spray Basil & Lavender 48H Antiperspirant Deodorant

Drug Facts

Active ingredient

Aluminum Chlorohydrate (23.3%)

Purpose

antiperspirant

Uses

reduces underarm wetness

Warnings

• FLAMMABLE. DO NOT USE NEAR HEAT, FLAME, OR WHILE SMOKING. CAN CAUSE SERIOUS INJURY OR DEATH
• Keep away from face and mouth to avoid breathing in.
• Avoid spraying in eyes. Contents under pressure. Do not puncture or incinerate. Do not expose to heat or store at temperatures above 120°F/50°C or in enclosed places that could overheat
• Do not use on broken skin. Stop use if rash or irritation occurs.
• Ask a doctor before using if you have kidney disease.
• USE ONLY AS DIRECTED. INTENTIONAL MISUSE BY DELIBERATELY CONCENTRATING AND INHALING THE CONTENTS CAN BE HARMFUL OR FATAL.
Help stop inhalation abuse. For information visit www.inhalant.org

• KEEP OUT OF REACH OF CHILDREN

Directions

apply to underarms only

Inactive ingredients

Butane, Cyclopentasiloxane, I Hydrofluorocarbon 152a, Isobutane, PPG-14 Butyl Ether, Fragrance (Parfum), Disteardimonium Hectorite, Propane, BHT, Caprylic/Capric Triglyceride, Sodium Starch Octenylsuccinate, Propylene Carbonate, Maltodextrin, Hydrated Silica, Hydrolyzed Corn Starch Octenylsuccinate, Gelatin Crosspolymer, Silica, Cellulose Gum, Sodium Benzoate

Questions?

Call toll-free 1-866-334-7331